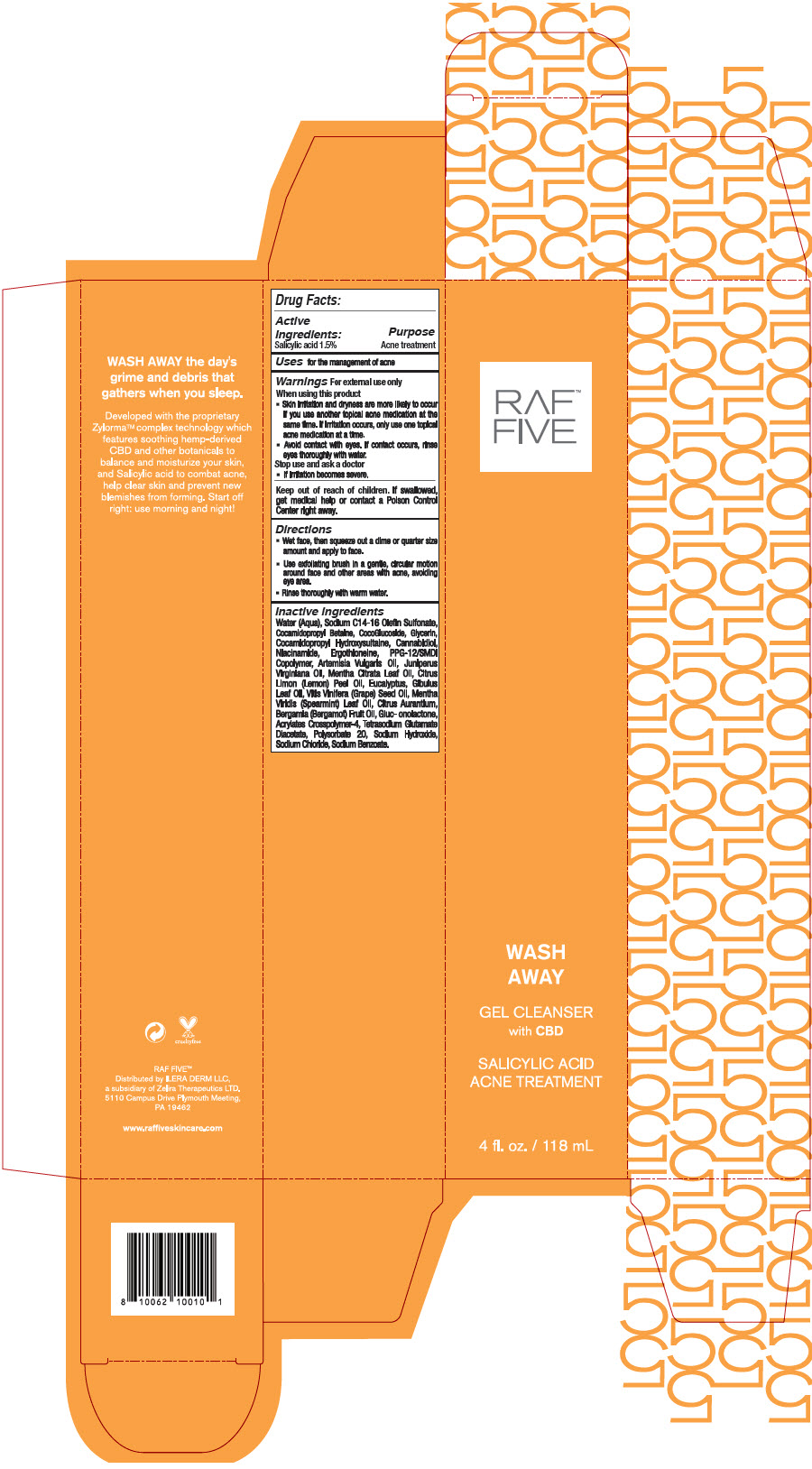 DRUG LABEL: RAF Five - Wash Away Salicylic Acid Gel Cleanser
NDC: 66163-4457 | Form: LIQUID
Manufacturer: Cosmetic Solutions LLC
Category: otc | Type: HUMAN OTC DRUG LABEL
Date: 20210827

ACTIVE INGREDIENTS: salicylic acid 1.5 g/100 mL
INACTIVE INGREDIENTS: Water; Sodium C14-16 Olefin Sulfonate; Cocamidopropyl Betaine; Coco Glucoside; Glycerin; Cocamidopropyl Hydroxysultaine; Cannabidiol; Niacinamide; Ergothioneine; PPG-12/SMDI Copolymer; Artemisia Vulgaris Top Oil; Juniperus Virginiana Oil; Lemon Oil, Cold Pressed; Eucalyptus Gum; Grape Seed Oil; Spearmint Oil; Bergamot Oil; Gluconolactone; Tetrasodium Glutamate Diacetate; Polysorbate 20; Sodium Hydroxide; Sodium Benzoate

RAF™ Five - Wash Away Salicylic Acid Gel Cleanser

Drug Facts:

Active Ingredients

Salicylic acid 1.5%

Purpose

Acne treatment

Uses

for the management of acne

Warnings

For external use only

When using this product

- Skin irritation and dryness are more likely to occur if you use another topical acne medication at the same time. If irritation occurs, only use one topical acne medication at a time.
- Avoid contact with eyes. If contact occurs, rinse eyes thoroughly with water.

Stop use and ask a doctor

- If irritation becomes severe.

Keep out of reach of children. If swallowed, get medical help or contact a Poison Control Center right away.

Directions

- Wet face, then squeeze out a dime or quarter size amount and apply to face.
- Use exfoliating brush in a gentle, circular motion around face and other areas with acne, avoiding eye area.
- Rinse thoroughly with warm water.

Inactive ingredients

Water (Aqua), Sodium C14-16 Olefin Sulfonate, Cocamidopropyl Betaine, CocoGlucoside, Glycerin, Cocamidopropyl Hydroxysultaine, Cannabidiol, Niacinamide, Ergothioneine, PPG-12/SMDI Copolymer, Artemisia Vulgaris Oil, Juniperus Virginiana Oil, Mentha Citrata Leaf Oil, Citrus Limon (Lemon) Peel Oil, Eucalyptus, Glbulus Leaf Oil, Vitis Vinifera (Grape) Seed Oil, Mentha Viridis (Spearmint) Leaf Oil, Citrus Aurantium, Bergamia (Bergamot) Fruit Oil, Gluc- onolactone, Acrylates Crosspolymer-4, Tetrasodium Glutamate Diacetate, Polysorbate 20, Sodium Hydroxide, Sodium Chloride, Sodium Benzoate.

Distributed by ILERA DERM LLC,
a subsidiary of Zelira Therapeutics LTD.
5110 Campus Drive Plymouth Meeting,
PA 19462

PRINCIPAL DISPLAY PANEL - 118 mL Tube Carton

RAF™
FIVE

WASH
AWAY

GEL CLEANSER
with CBD

SALICYLIC ACID
ACNE TREATMENT

4 fl. oz. / 118 mL